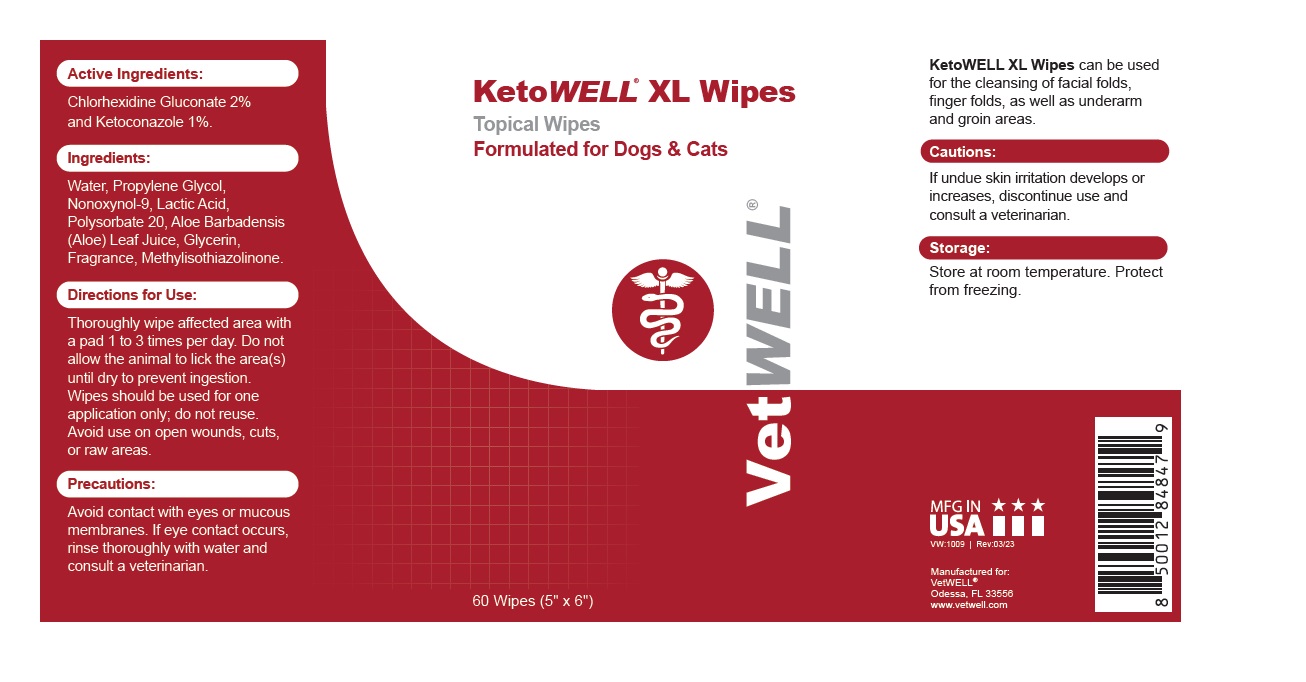 DRUG LABEL: KetoWELL XL Wipes
NDC: 86090-006 | Form: CLOTH
Manufacturer: Pet MD Brands, LLC
Category: animal | Type: OTC ANIMAL DRUG LABEL
Date: 20230907

ACTIVE INGREDIENTS: CHLORHEXIDINE GLUCONATE 2 g/100 mL; KETOCONAZOLE 1 g/100 mL
INACTIVE INGREDIENTS: WATER; PROPYLENE GLYCOL; NONOXYNOL-9; LACTIC ACID, UNSPECIFIED FORM; POLYSORBATE 20; ALOE VERA LEAF; GLYCERIN; METHYLISOTHIAZOLINONE

KetoWELL® XL Wipes

Active Ingredients:

Chlorhexidine Gluconate 2% and Ketoconazole 1%.

INDICATIONS AND USAGE

KetoWELL XL Wipes can be used for the cleansing of facial folds, finger folds, as well as underarm and groin areas.

Ingredients:

Water, Propylene Glycol, Nonoxynol-9, Lactic Acid, Polysorbate 20, Aloe Barbadensis (Aloe) Leaf Juice, Glycerin, Fragrance, Methylisothiazolinone.

Directions for Use:

Thoroughly wipe affected area with a pad 1 to 3 times per day. Do not allow the animal to lick the area(s) until dry to prevent ingestion.
Wipes should be used for one application only; do not reuse. Avoid use on open wounds, cuts, or raw areas.

Precautions:

Avoid contact with eyes or mucous membranes. If eye contact occurs, rinse thoroughly with water and consult a veterinarian.

Cautions:

If undue skin irritation develops or increases, discontinue use and consult a veterinarian.

Storage:

Store at room temperature. Protect from freezing.

Formulated for Dogs & Cats

MFG IN USA

Manufactured for:
VetWELL®
Odessa, FL 33556
www.vetwell.com